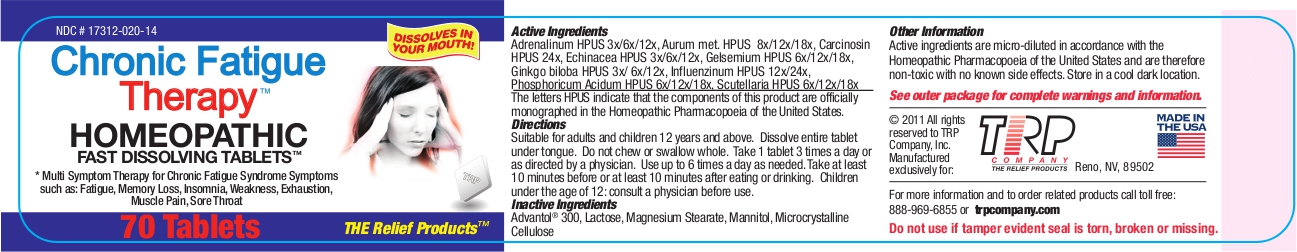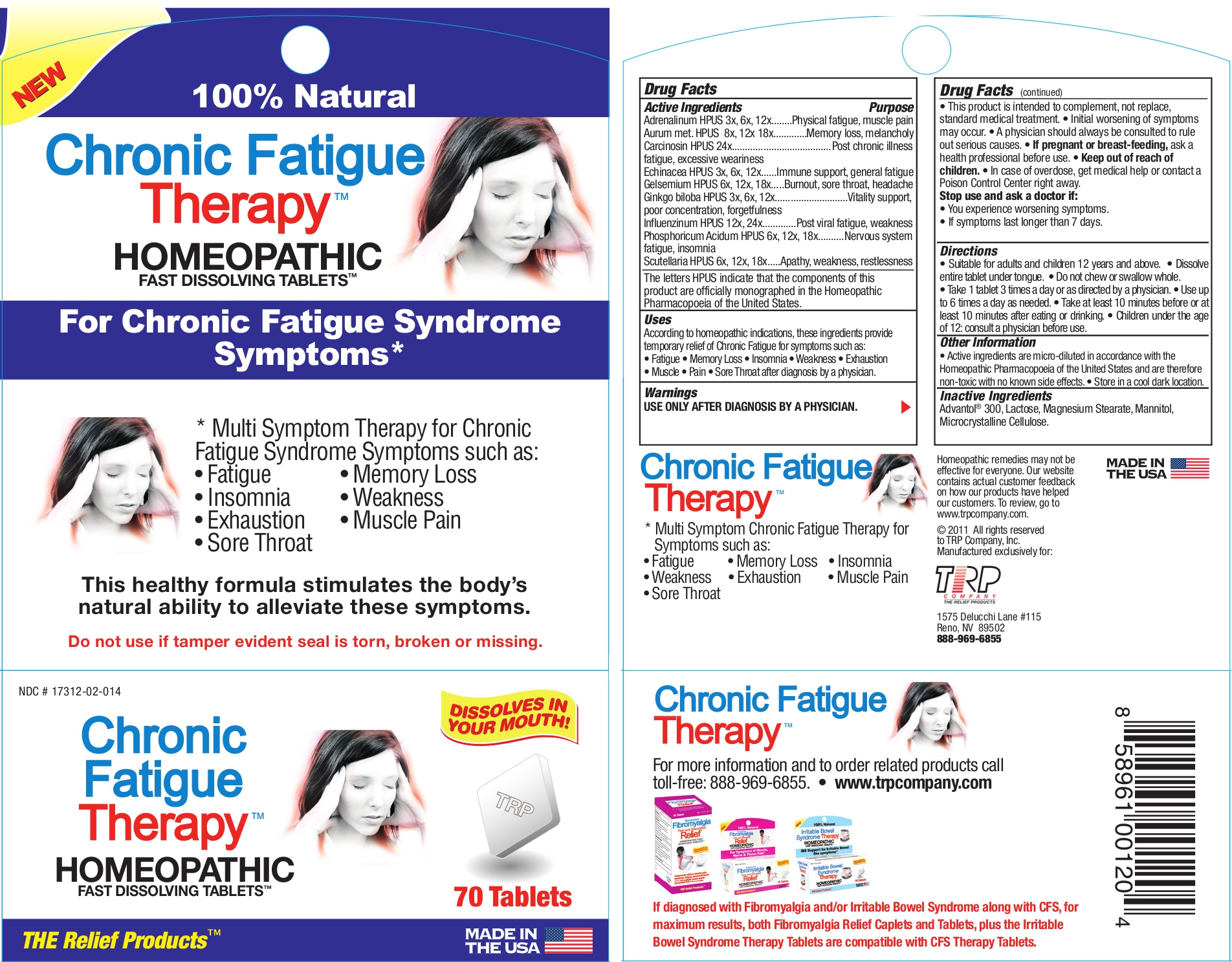 DRUG LABEL: Chronic Fatigue Therapy
NDC: 17312-020 | Form: TABLET, ORALLY DISINTEGRATING
Manufacturer: TRP Company
Category: homeopathic | Type: HUMAN OTC DRUG LABEL
Date: 20121030

ACTIVE INGREDIENTS: EPINEPHRINE 3 [hp_X]/1 1; GOLD 8 [hp_X]/1 1; HUMAN BREAST TUMOR CELL 24 [hp_X]/1 1; ECHINACEA, UNSPECIFIED 3 [hp_X]/1 1; GELSEMIUM SEMPERVIRENS ROOT 6 [hp_X]/1 1; GINKGO 3 [hp_X]/1 1; INFLUENZA B VIRUS 12 [hp_X]/1 1; PHOSPHORIC ACID 6 [hp_X]/1 1; SCUTELLARIA LATERIFLORA TOP 6 [hp_X]/1 1
INACTIVE INGREDIENTS: MANNITOL; SORBITOL; CROSPOVIDONE; CELLULOSE, MICROCRYSTALLINE; COPOVIDONE; SILICON DIOXIDE; LACTOSE; MAGNESIUM STEARATE

Chronic Fatigue Therapy™ Homeopathic Fast Dissolving Tablets

Active Ingredients |  | Purpose
Adrenalinum HPUS | 3x, 6x, 12x | Physical fatigue, muscle pain
Aurum met. HPUS | 8x, 12x 18x | Memory loss, melancholy
Carcinosin HPUS | 24x | Post chronic illness fatigue, excessive weariness
Echinacea HPUS | 3x, 6x, 12x | Immune support, general fatigue
Gelsemium HPUS | 6x, 12x, 18x | Burnout, sore throat, headache
Ginkgo biloba HPUS | 3x, 6x, 12x | Vitality support, poor concentration, forgetfulness
Influenzinum HPUS | 12x, 24x | Post viral fatigue, weakness
Phosphoricum Acidum HPUS | 6x, 12x, 18x | Nervous system fatigue, insomnia
Scutellaria HPUS | 6x, 12x, 18x | Apathy, weakness, restlessness

The letters HPUS indicate that the components of this product are officially monographed in the Homeopathic Pharmacopoeia of the United States.

Uses

According to homeopathic indications, these ingredients provide temporary relief of Chronic Fatigue for symptoms such as: • Fatigue • Memory Loss • Insomnia • Weakness • Exhaustion • Muscle • Pain • Sore Throat after diagnosis by a physician.

Warnings

USE ONLY AFTER DIAGNOSIS BY A PHYSICIAN.

- This product is intended to complement, not replace, standard medical treatment.
- Initial worsening of symptoms may occur.
- A physician should always be consulted to rule out serious causes.
- In case of overdose, get medical help or contact a Poison Control Center right away.

Stop use and ask a doctor if:

- You experience worsening symptoms.
- If symptoms last longer than 7 days.

PREGNANCY OR BREAST FEEDING

If pregnant or breast-feeding, ask a health professional before use.

Directions

- Suitable for adults and children 12 years and above.
- Dissolve entire tablet under tongue.
- Do not chew or swallow whole.
- Take 1 tablet 3 times a day or as directed by a physician.
- Use up to 6 times a day as needed.
- Take at least 10 minutes before or at least 10 minutes after eating or drinking.
- Children under the age of 12: consult a physician before use.

Other information

- Active ingredients are micro-diluted in accordance with the Homeopathic Pharmacopoeia of the United States and are therefore non-toxic with no known side effects.
- Store in a cool dark location.

Inactive Ingredients

Advantol® 300, Lactose, Magnesium Stearate, Mannitol, Microcrystalline Cellulose.

QUESTIONS

For more information and to order related products call toll free: 888-969-6855 or trpcompany.com